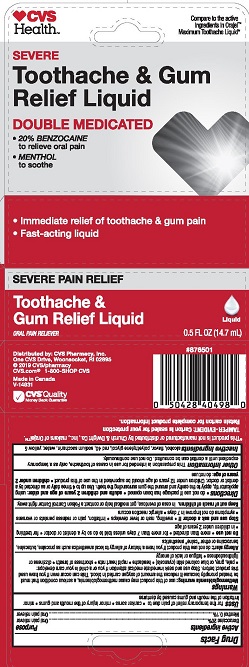 DRUG LABEL: 2x Med Liq
NDC: 49354-375 | Form: LIQUID
Manufacturer: CSR Cosmetic Solutions
Category: otc | Type: HUMAN OTC DRUG LABEL
Date: 20210902

ACTIVE INGREDIENTS: BENZOCAINE 20 mg/100 mL; MENTHOL, UNSPECIFIED FORM 0.1 mg/100 mL
INACTIVE INGREDIENTS: ALCOHOL; WATER; FD&C YELLOW NO. 5; POLYETHYLENE GLYCOL 400; SACCHARIN SODIUM; FD&C RED NO. 40

5820375 CVS 2x Med Liq (CSR)

ACTIVE INGREDIENT

Benzocaine 20%

Menthol 0.1%

PURPOSE

Oral anesthetic

Oral anesthetic

INDICATIONS AND USAGE

temporarily relieves pain associated with the following mouth and gum irritations: * toothache * sore gums * canker sores * braces * minor dental procedures

WARNINGS

Methemoglobinemia warning: use of this product may cause methemoglobinemia, a serious condition that must be treated prompty because it reduces the amount of oxygen carried in blood. This can occur even if you have used this product before. Stop use and seek immediate medical attention if you or a child in your care develops: * pale, gray, or blue colored skin (cyanosis) * headache * rapid heart rate * shortness of breath * dizziness or lightheadedness * fatigue or lack of energy

Allergy alert: do not use this product if you have a history of allergy to local anesthetics such as procaine, butacaine, benzocaine, or other "caine" anesthetics

Do not use * more than directed * for more than 7 days unless told to do so by a dentist or doctor * for teething * in children under 2 years of age

Stop use and ask a doctor if * swelling, rash or fever develops * irritation, pain or redness persists or worsens * symptoms do not improve in 7 days * allergic reaction occurs

Keep out of reach of children. In case of overdose, get medical help or contact a Poison Control Center right away.

DOSAGE AND ADMINISTRATION

Adults and children 2 years of age and older: * apply to affected area using applicator tip * use up to 4 times daily or as directed by a dentist or doctor * children under 12 years of age should be supervised in the use of this product. children under 2 years of age: do not use

do not use if package has been opened * store ar 20-25°C (68-77°F)

INACTIVE INGREDIENT

alcohol, flavor, polyethylene glycol, red 40, sodium saccharin, water, yellow 5